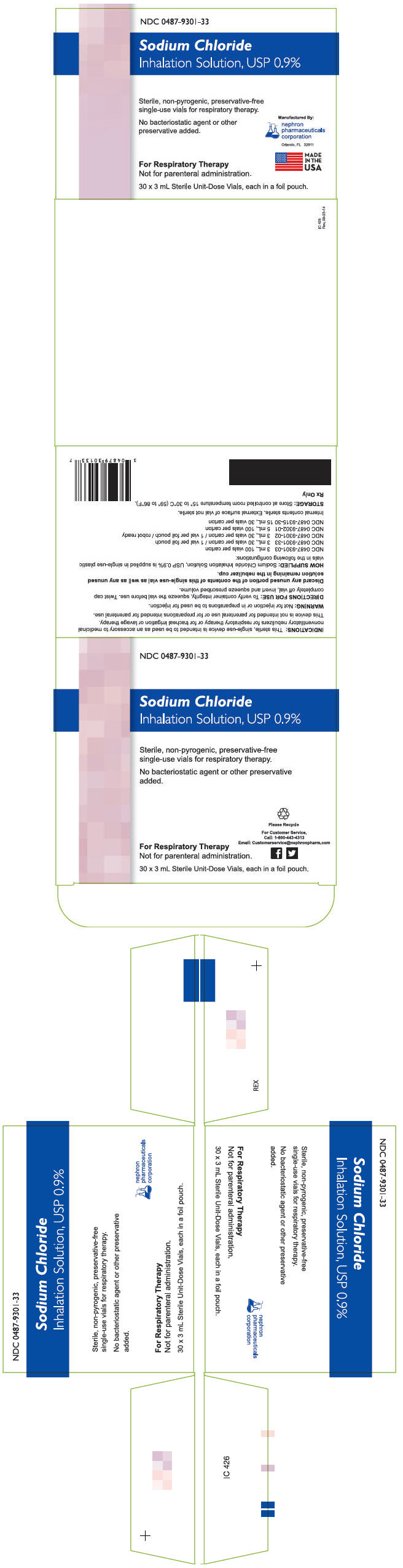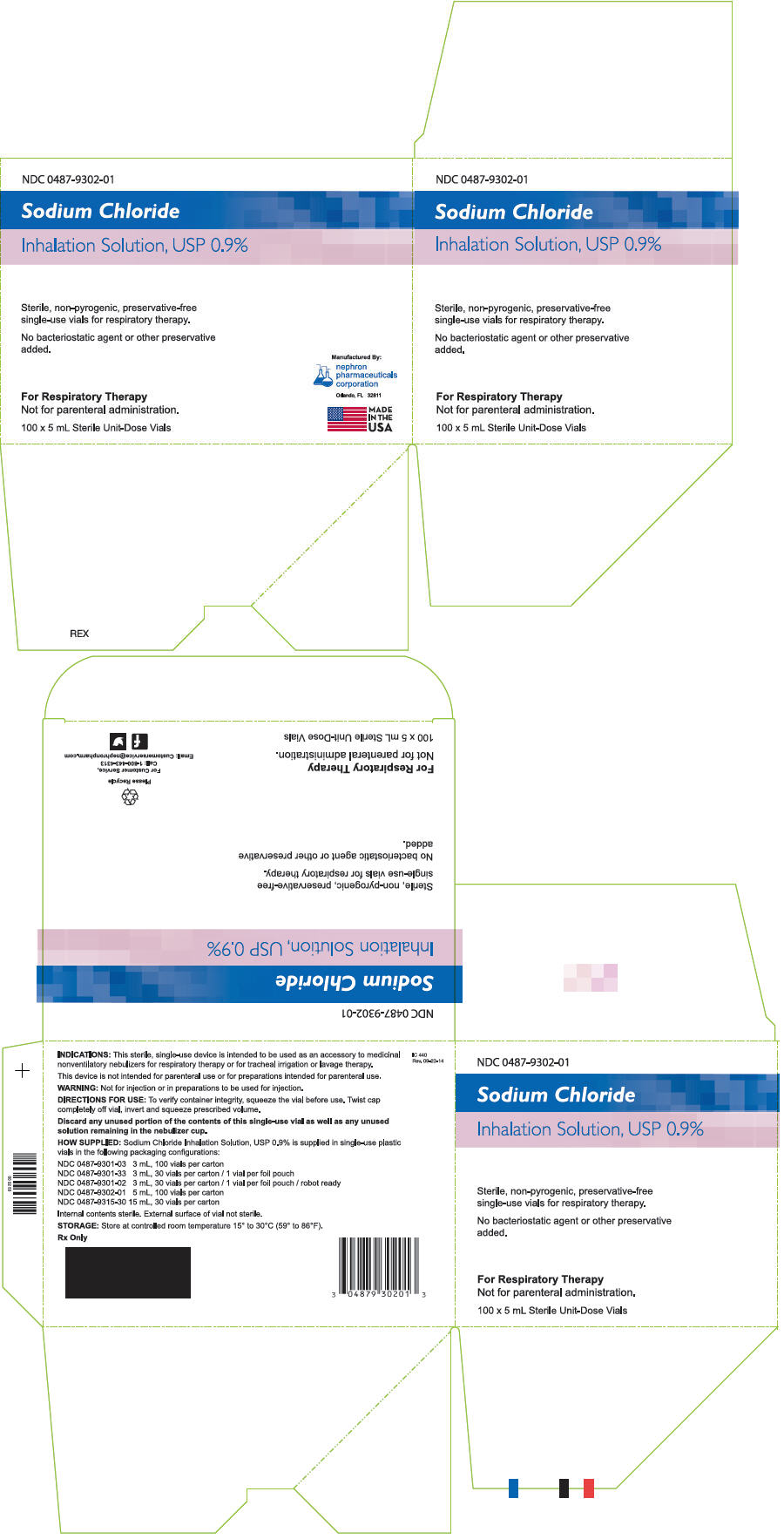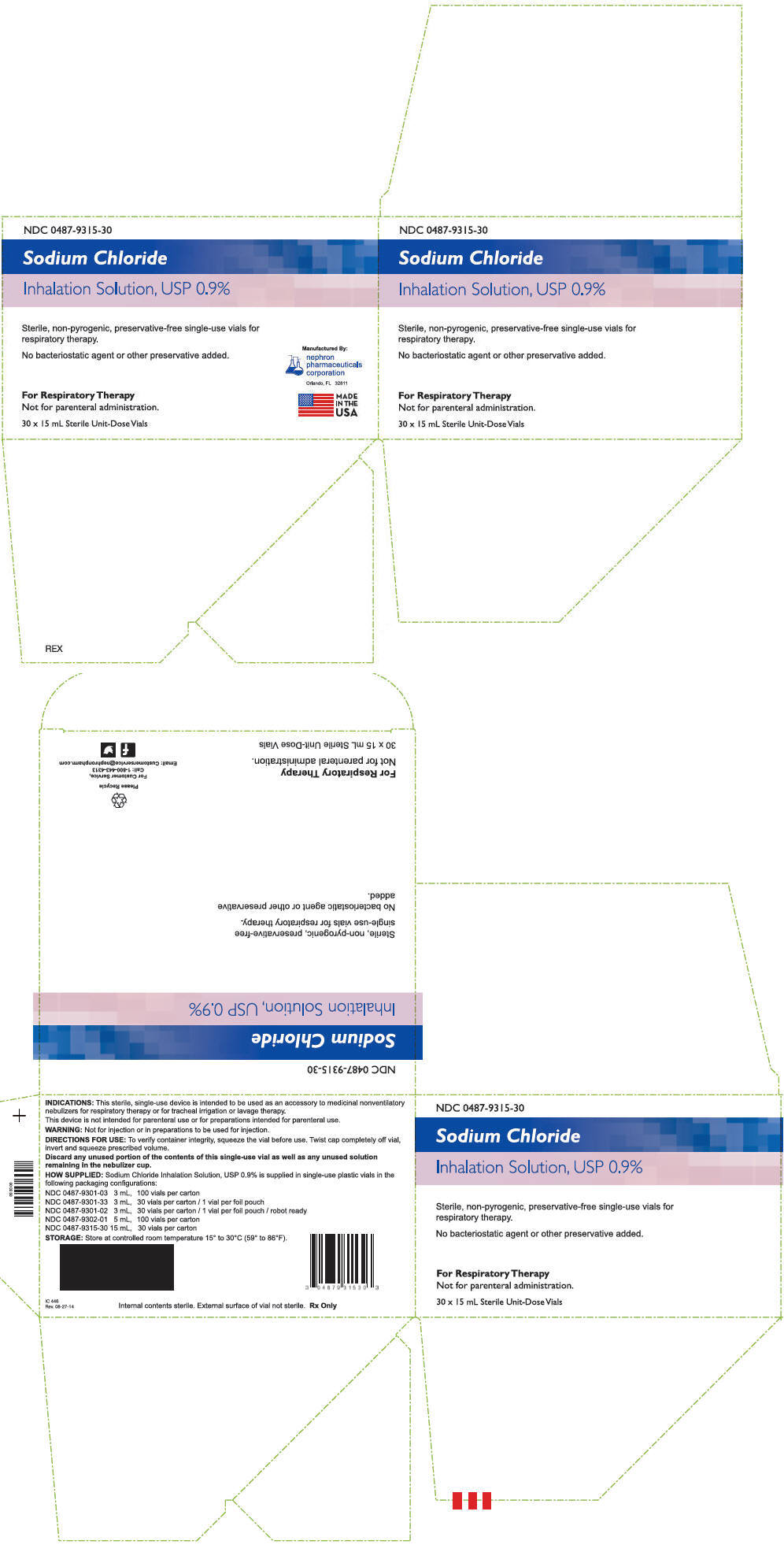 DRUG LABEL: Sodium Chloride
NDC: 0487-9301
Manufacturer: Nephron Pharmaceuticals Corporation
Category: other | Type: MEDICAL DEVICE
Date: 20150130

ACTIVE INGREDIENTS: Sodium Chloride 9 mg/1 mL
INACTIVE INGREDIENTS: Water

Sodium Chloride Inhalation Solution, USP 0.9%

Sodium Chloride Inhalation Solution, USP 0.9% 3 mL

NDC 0487-9301-33

Sodium Chloride
Inhalation Solution, USP 0.9%

Sterile, non-pyrogenic, preservative-free
single-use vials for respiratory therapy.

No bacteriostatic agent or other
preservative added.

MADE
IN THE
USA

For Respiratory Therapy
Not for parenteral administration.

nephron
pharmaceuticals
corporation
Orlando, FL 32811

30 × 3 mL Sterile Unit-Dose Vials, each in a foil pouch.

INDICATIONS: This sterile, single-use device is intended to be used as an accessory to medicinal nonventilatory nebulizers for respiratory therapy or for tracheal irrigation or lavage therapy.

This device is not intended for parenteral use or for preparations intended for parenteral use.

WARNING: Not for injection or in preparations to be used for injection.

DIRECTIONS FOR USE: To verify container integrity, squeeze the vial before use. Twist cap completely off vial, invert and squeeze prescribed volume.

Discard any unused portion of the contents of this single-use vial as well as any unused solution remaining in the nebulizer cup.

HOW SUPPLIED: Sodium Chloride Inhalation Solution, USP 0.9% is supplied in single-use plastic vials in the following configurations:

NDC 0487-9301-03 3 mL, 100 vials per carton
NDC 0487-9301-33 3 mL, 30 vials per carton / 1 vial per foil pouch
NDC 0487-9301-02 3 mL, 30 vials per carton / 1 vial per foil pouch / robot ready
NDC 0487-9302-01 5 mL, 100 vials per carton
NDC 0487-9315-30 15 mL, 30 vials per carton

Internal contents sterile. External surface of vial not sterile.

STORAGE: Store at controlled room temperature 15° to 30°C (59° to 86°F).

Rx Only

Please Recycle

IC 426
Rev. 09-23-14

Sodium Chloride Inhalation Solution, USP 0.9% 5 mL

NDC 0487-9302-01

Sodium Chloride
Inhalation Solution, USP 0.9%

Sterile, non-pyrogenic, preservative-free
single-use vials for respiratory therapy.

No bacteriostatic agent or other preservative
added.

For Respiratory Therapy
Not for parenteral administration.

100 × 5 mL Sterile Unit-Dose Vials

Manufactured By:
nephron
pharmaceuticals
corporation
Orlando, FL 32811

INDICATIONS: This sterile, single-use device is intended to be used as an accessory to medicinal nonventilatory nebulizers for respiratory therapy or for tracheal irrigation or lavage therapy.

This device is not intended for parenteral use or for preparations intended for parenteral use.

WARNING: Not for injection or in preparations to be used for injection.

DIRECTIONS FOR USE: To verify container integrity, squeeze the vial before use. Twist cap completely off vial, invert and squeeze prescribed volume.

Discard any unused portion of the contents of this single-use vial as well as any unused solution remaining in the nebulizer cup.

HOW SUPPLIED: Sodium Chloride Inhalation Solution, USP 0.9% is supplied in single-use plastic vials in the following configurations:

NDC 0487-9301-03 3 mL, 100 vials per carton
NDC 0487-9301-33 3 mL, 30 vials per carton / 1 vial per foil pouch
NDC 0487-9301-02 3 mL, 30 vials per carton / 1 vial per foil pouch / robot ready
NDC 0487-9302-01 5 mL, 100 vials per carton
NDC 0487-9315-30 15 mL, 30 vials per carton

Internal contents sterile. External surface of vial not sterile.

STORAGE: Store at controlled room temperature 15° to 30°C (59° to 86°F).

Rx Only

Please Recycle

IC 440
Rev. 09-23-14

Sodium Chloride Inhalation Solution, USP 0.9% 15 mL

NDC 0487-9315-30

Sodium Chloride
Inhalation Solution, USP 0.9%

Sterile, non-pyrogenic, preservative-free single-use vials for
respiratory therapy.

No bacteriostatic agent or other preservative added.

For Respiratory Therapy
Not for parenteral administration.

30 × 15 mL Sterile Unit-Dose Vials

Manufactured By:
nephron
pharmaceuticals
corporation
Orlando, FL 32811

MADE
IN THE
USA

INDICATIONS: This sterile, single-use device is intended to be used as an accessory to medicinal nonventilatory nebulizers for respiratory therapy or for tracheal irrigation or lavage therapy.

This device is not intended for parenteral use or for preparations intended for parenteral use.

WARNING: Not for injection or in preparations to be used for injection.

DIRECTIONS FOR USE: To verify container integrity, squeeze the vial before use. Twist cap completely off vial, invert and squeeze prescribed volume.

Discard any unused portion of the contents of this single-use vial as well as any unused solution remaining in the nebulizer cup.

HOW SUPPLIED: Sodium Chloride Inhalation Solution, USP 0.9% is supplied in single-use plastic vials in the following packaging configurations:

NDC 0487-9301-03 3 mL, 100 vials per carton
NDC 0487-9301-33 3 mL, 30 vials per carton / 1 vial per foil pouch
NDC 0487-9301-02 3 mL, 30 vials per carton / 1 vial per foil pouch / robot ready
NDC 0487-9302-01 5 mL, 100 vials per carton
NDC 0487-9315-30 15 mL, 30 vials per carton

STORAGE: Store at controlled room temperature 15° to 30°C (59° to 86°F).

Internal contents sterile. External surface of vial not sterile.
Rx Only

IC 446
Rev. 08-27-14